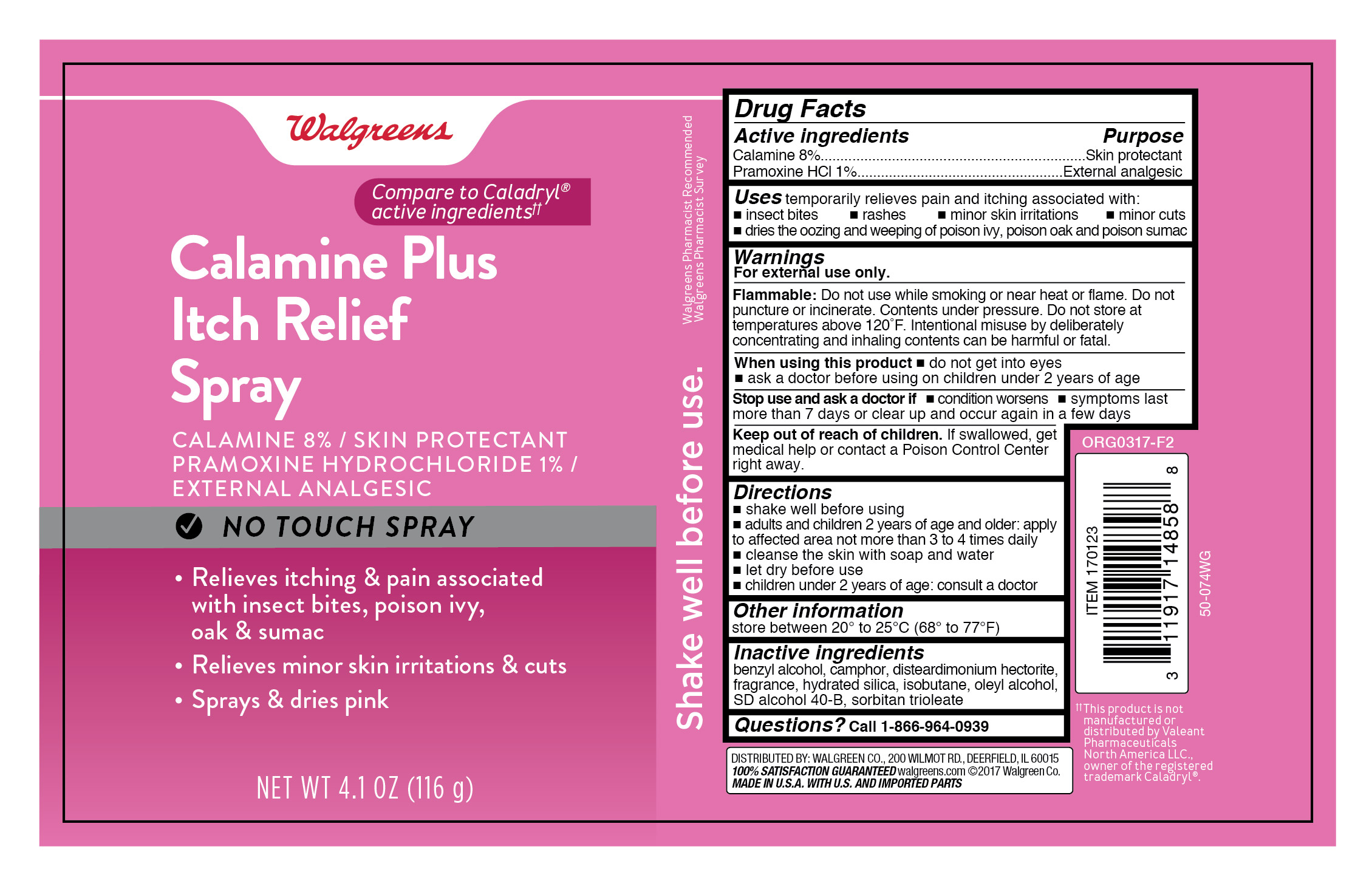 DRUG LABEL: Calamine Plus Pramoxine HCl
NDC: 0363-8588 | Form: AEROSOL, SPRAY
Manufacturer: Walgreens Company
Category: otc | Type: HUMAN OTC DRUG LABEL
Date: 20251106

ACTIVE INGREDIENTS: FERRIC OXIDE RED 0.345 mg/177 mL; ZINC OXIDE 24.16 mg/177 mL; PRAMOXINE HYDROCHLORIDE 2.72 mg/177 mL
INACTIVE INGREDIENTS: BENZYL ALCOHOL; CAMPHOR (SYNTHETIC); HYDRATED SILICA; ISOBUTANE; OLEYL ALCOHOL; SORBITAN TRIOLEATE; DISTEARDIMONIUM HECTORITE; ALCOHOL

Walgreens Calamine Plus Spray

Active ingredient

Calamine 8%
Pramoxine HCl 1%

Purpose

Skin protectant
External analgesic

Uses

temporarily relieves pain and itching associated with:

- insect bites
- rashes
- minor skin irritations
- minor cuts
- dries the oozing and weeping of poison ivy, poison oak and poison sumac

Warnings

For external use only. Use only as directed. Intentional misuse by deliberately concentrating and inhailing contents can be harmful or fatal.

Flammable:

Do not use while smoking or near heat or flame. Do not puncture or incinerate. Contents under pressure. Do not store at temperatures above 120°F.

When using this product

- do not get into eyes
- ask a doctor before using on children under 2 years of age

Stop use and ask a doctor if

- conditions worsens
- symtomps last more than 7 days or clear up and occur again in a few days

Keep out of reach of children.

If swallowed, get medical help or contact a Poison Control Center right away.

Directions

- shake well before using
- adults and children 2 years of age and older: apply to affected area not more than 3 to 4 times daily
- cleanse the skin with soap and water
- let dry before use
- children under 2 years of age: consult a doctor

Other information

store between 20° to 25°C (68° to 77°F)

Inactive ingredients

benzyl alcohol, camphor, disteardimonium hectorite, fragrance, hydrated silica, isobutane, oleyl alcohol, SD alcohol 40-B, sorbitan trioleate

Questions?

Call 1-866-964-0939

Principal Display Panel

Walgreens

Calamine Plus

Itch Relief

Spray

CALAMINE 8% / SKIN PROTECTANT

PRAMOXINE HYDROCHLORIDE 1% /

EXTERNAL ANALGESIC

NO TOUCH SPRAY

- Relieves itching and pain associated with insect bites, poison ivy, oak & sumac
- Relieves minor skin irritations & cuts
- Sprays & dries pink

NET WT 4.1 OZ (116g)